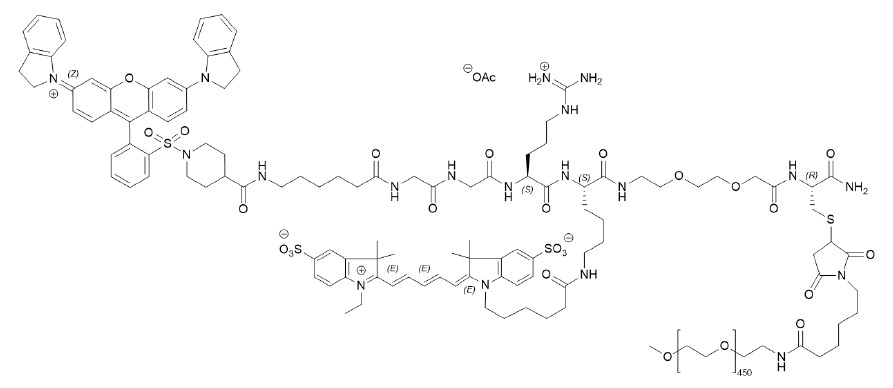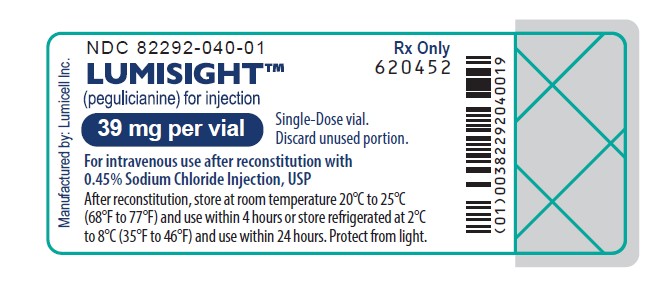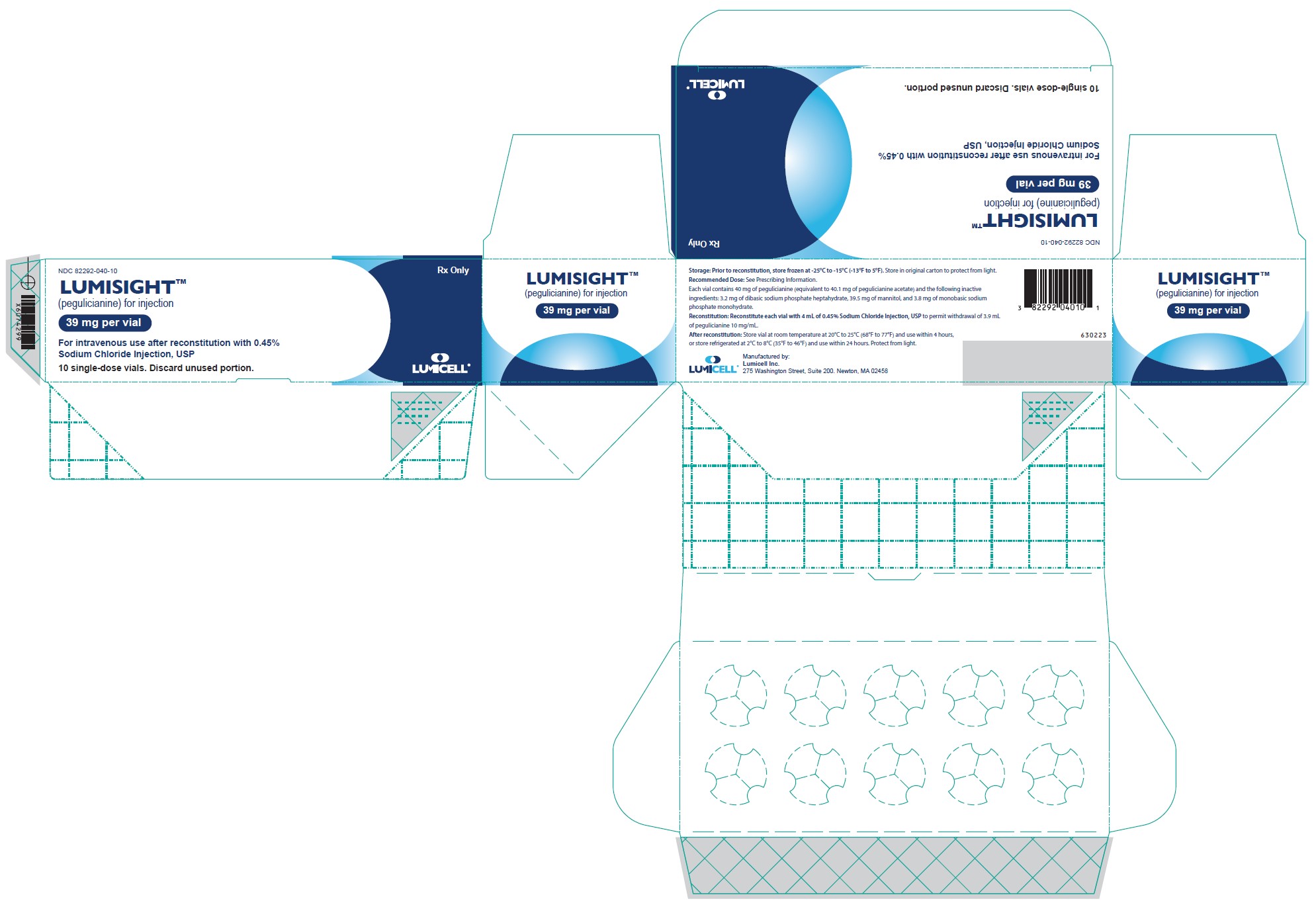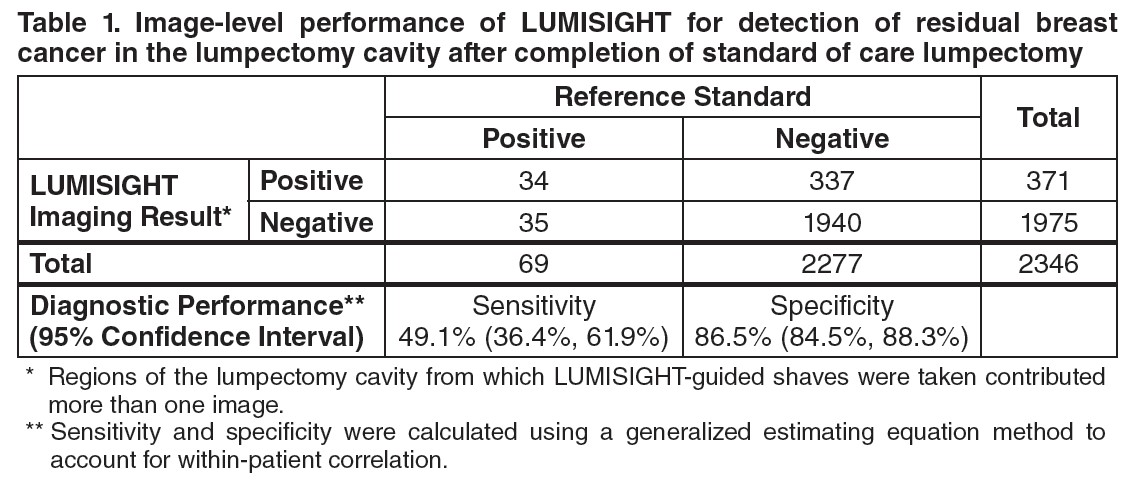 DRUG LABEL: LUMISIGHT
NDC: 82292-040 | Form: Injection, powder, lyophilized, for solution
Manufacturer: Lumicell, Inc.
Category: prescription | Type: HUMAN PRESCRIPTION DRUG LABEL
Date: 20240603

ACTIVE INGREDIENTS: PEGULICIANINE 10 mg/1 mL
INACTIVE INGREDIENTS: MANNITOL; SODIUM PHOSPHATE, MONOBASIC, MONOHYDRATE; SODIUM PHOSPHATE, DIBASIC, HEPTAHYDRATE

HIGHLIGHTS OF PRESCRIBING INFORMATION

These highlights do not include all the information needed to use LUMISIGHT safely and effectively. See full prescribing information for LUMISIGHT.
LUMISIGHT™ (pegulicianine) for injection, for intravenous use
Initial U.S. Approval: 2024

WARNING: ANAPHYLAXIS AND OTHER SERIOUS HYPERSENSITIVITY REACTIONS

See full prescribing information for complete boxed warning.

Serious hypersensitivity reactions, including anaphylaxis, can occur during or following administration. Anaphylaxis has occurred in 4/726 (0.6%) of patients in clinical studies. Before LUMISIGHT administration, assess all patients for any history of hypersensitivity reaction to contrast media or products containing polyethylene glycol (PEG). Always have emergency resuscitation drugs, equipment, and trained personnel available. Monitor all patients for hypersensitivity reactions. If a hypersensitivity reaction is suspected, immediately discontinue the injection and initiate appropriate therapy. (5.1).

1 INDICATIONS AND USAGE

LUMISIGHT is an optical imaging agent indicated for fluorescence imaging in adults with breast cancer as an adjunct for the intraoperative detection of cancerous tissue within the resection cavity following removal of the primary specimen during lumpectomy surgery. (1)

2 DOSAGE AND ADMINISTRATION

- Recommended dose of LUMISIGHT is 1 mg/kg by intravenous injection over 3 minutes administered 2 hours to 6 hours prior to imaging. (2.1)
- See Full Prescribing Information for instructions on preparation, administration, and imaging. (2.2, 2.3, 2.4)

3 DOSAGE FORMS AND STRENGTHS

For injection: lyophilized powder in a single-dose vial delivering 39 mg of pegulicianine after reconstitution. (3)

4 CONTRAINDICATIONS

History of hypersensitivity reaction to pegulicianine. (4)

5 WARNINGS AND PRECAUTIONS

- Risk of Misdiagnosis: Absence of signal in the surgical field does not rule out the presence of cancer. Positive signal may be seen in non-cancerous tissue. (5.2)
- Interference from Dyes Used for Sentinel Lymph Node Mapping: Avoid administration of dyes before imaging the lumpectomy cavity in patients receiving LUMISIGHT. (5.3, 7)

6 ADVERSE REACTIONS

Most common adverse reactions (≥1%) were hypersensitivity and chromaturia. (6.1)

To report SUSPECTED ADVERSE REACTIONS, contact Lumicell at 1-833-458-6387 or FDA at 1-800-FDA-1088 or www.fda.gov/medwatch.

FULL PRESCRIBING INFORMATION

WARNING: ANAPHYLAXIS AND OTHER SERIOUS HYPERSENSITIVITY REACTIONS

Serious hypersensitivity reactions, including anaphylaxis, can occur during or following administration of LUMISIGHT. Anaphylaxis occurred in 4/726 (0.6%) of patients in clinical studies. Signs and symptoms associated with other hypersensitivity reactions included pruritus, urticaria, hypotension, lip swelling, erythema, anxiety, chest pain, cyanosis, dizziness, dyspnea, headache, hypoesthesia, hyperventilation, maculopapular rash, nausea, paresthesia, visual changes, and vomiting.

- Before LUMISIGHT administration, assess all patients for any history of hypersensitivity reaction to contrast media or products containing polyethylene glycol (PEG).
- Always have emergency resuscitation drugs, equipment, and trained personnel promptly available.
- Monitor all patients for hypersensitivity reactions. If a hypersensitivity reaction is suspected, immediately discontinue the injection and initiate appropriate therapy.
- LUMISIGHT is contraindicated in patients with a history of hypersensitivity reactions to pegulicianine [see Warning and Precautions (5.1)].

1 INDICATIONS AND USAGE

LUMISIGHT is indicated for fluorescence imaging in adults with breast cancer as an adjunct for the intraoperative detection of cancerous tissue within the resection cavity following removal of the primary specimen during lumpectomy surgery.

2 DOSAGE AND ADMINISTRATION

2.1 Recommended Dose

The recommended dose of LUMISIGHT is 1 mg/kg actual body weight by intravenous injection over 3 minutes administered 2 hours to 6 hours prior to imaging.

2.2 Preparation of LUMISIGHT

Important Preparation Information

- Prior to reconstitution, store vials in the freezer at -25°C to -15°C (-13°F to 5°F). Protect from light.
- Use aseptic technique for the preparation of LUMISIGHT.
- The recommended dose depends on the individual patient’s weight. Multiple vials of LUMISIGHT may need to be reconstituted to achieve the individual patient dose.
- Only use 0.45% Sodium Chloride Injection, USP for reconstitution of LUMISIGHT to prevent high osmolality.

Preparation Instructions

1. Calculate the dose (1 mg/kg) and the total volume (mL) of LUMISIGHT based on the individual patient’s weight.
2. Obtain the number of vials required to administer the patient dose.
3. Allow the vials to acclimate to room temperature between 20°C to 25°C (68°F to 77°F) for approximately 5 minutes.
4. Reconstitute each vial of LUMISIGHT with 4 mL of 0.45% Sodium Chloride Injection, USP to permit withdrawal of 3.9 mL of LUMISIGHT 10 mg/mL.
5. Visually inspect the reconstituted solution. It should be a clear, dark blue-colored solution free of particulate matter. Discard if there is any discoloration or particulate matter.
6. If not immediately used, store the reconstituted LUMISIGHT vial at room temperature at 20°C to 25°C (68°F to 77°F) and use within 4 hours, or store the reconstituted LUMISIGHT vial in the refrigerator at 2°C to 8°C (35°F to 46°F) and use within 24 hours. Protect from light.
7. Each vial of LUMISIGHT is for a single dose. Discard unused portion.

2.3 Administration

- Withdraw the calculated volume from the appropriate number of vials into one syringe for administration of one single dose of 1 mg/kg. Verify that the syringe contains the intended volume.
- Prior to administration of LUMISIGHT, flush the peripheral intravenous (IV) line with 10 mL to 20 mL of 0.9% Sodium Chloride Injection, USP.
- Administer LUMISIGHT as an IV injection over 3 minutes beginning 2 hours to 6 hours prior to imaging with the Lumicell DVS.
- After administration of LUMISIGHT, flush the IV line with 10 mL to 20 mL of 0.9% Sodium Chloride Injection, USP.

2.4 Imaging

LUMISIGHT is used with the Lumicell Direct Visualization System (DVS) or other fluorescence imaging device that is FDA-approved for specific use with pegulicianine in the indicated population. The device provides illumination to excite the fluorescent components of pegulicianine and collects images showing pegulicianine’s fluorescence emission. Regions suspected to contain cancerous tissue are highlighted as positive signals on the Lumicell DVS display [see Clinical Studies (14)].

Training on the use of the device is essential prior to employing the system in a lumpectomy procedure. Please refer to the device labeling for details on how to use the device and for training information.

3 DOSAGE FORMS AND STRENGTHS

For injection: dark blue lyophilized powder in a single-dose vial delivering 39 mg pegulicianine after reconstitution.

4 CONTRAINDICATIONS

LUMISIGHT is contraindicated in patients with a history of hypersensitivity reaction to pegulicianine. Reactions have included anaphylaxis [see Warning and Precautions (5.1)].

5 WARNINGS AND PRECAUTIONS

5.1 Anaphylaxis and Other Serious Hypersensitivity Reactions

Prepare for the possibility of drug hypersensitivity reactions (including anaphylaxis), which can occur during or following administration, and take the necessary precautions.

In clinical studies, 4 of 726 (0.6%) patients treated with LUMISIGHT experienced signs and symptoms consistent with anaphylaxis. The onset was during administration in three patients. Signs and symptoms associated with other hypersensitivity reactions included pruritus, urticaria, hypotension, lip swelling, erythema, anxiety, chest pain, cyanosis, dizziness, dyspnea, headache, hypoesthesia, hyperventilation, maculopapular rash, nausea, paresthesia, visual changes, and vomiting [see Adverse Reactions (6.1)].

Before LUMISIGHT administration, assess all patients for any history of hypersensitivity reaction to contrast media or products containing polyethylene glycol (PEG), as these patients may have an increased risk for hypersensitivity reaction to LUMISIGHT. In clinical studies, three out of four patients that experienced anaphylaxis did not have a history of hypersensitivity reaction to contrast media or products containing PEG.

Always have emergency resuscitation drugs, equipment, and trained personnel available. Monitor all patients for hypersensitivity reactions through symptom reporting, direct observation, and vital sign measurements. If a hypersensitivity reaction is suspected, immediately discontinue the injection and initiate appropriate therapy. LUMISIGHT is contraindicated in patients with a history of hypersensitivity reaction to pegulicianine [see Contraindications (4)].

5.2 Risk of Misdiagnosis

False positive and false negative findings may occur during use of LUMISIGHT to detect residual cancer. Absence of signal in the lumpectomy cavity does not rule out the presence of residual cancer. Additionally, positive signal has been observed in some non-cancerous tissue [see Clinical Studies (14)].

5.3 Interference from Dyes Used for Sentinel Lymph Node Mapping

Blue dyes used for sentinel lymph node (SLN) mapping procedures interfere with LUMISIGHT imaging. The potential of other dyes to interfere with LUMISIGHT imaging has not been evaluated. Avoid administration of dyes used for SLN mapping procedures before imaging the lumpectomy cavity in patients receiving LUMISIGHT [see Drug Interactions (7)].

6 ADVERSE REACTIONS

The following clinically important adverse reactions are described elsewhere in the labeling:

- Anaphylaxis and Other Serious Hypersensitivity Reactions [see Warnings and Precautions (5.1)]

6.1 Clinical Trials Experience

Because clinical trials are conducted under widely varying conditions, adverse reaction rates observed in the clinical trials of a drug cannot be directly compared to rates in the clinical trials of another drug and may not reflect the rates observed in practice.

The safety of LUMISIGHT was evaluated in 726 patients who received a single dose of 1 mg/kg of LUMISIGHT. Among these 726 patients, 703 (97%) had breast cancer and 23 (3%) had other types of cancer. The mean age of the patients was 62 years (range: 36 years to 95 years), and 98% of them were female. Distribution by race was 82% White, 7% Black or African American, 6% Asian, and 5% other or unreported. Distribution by ethnicity was 3% Hispanic/Latino, 93% non-Hispanic/Latino, and 4% unknown or unreported.

Adverse reactions occurring in ≥ 1% of patients receiving LUMISIGHT were hypersensitivity (1.4%, including anaphylaxis [4 out of 726]) and chromaturia (85%). Chromaturia resolved within 48 hours after administration in 93% of patients, with the longest time to resolution of 15 days.

Adverse reactions occurring in use < 1% of patients were skin discoloration after extravasation, nausea, dyspnea, pyrexia, and vomiting.

7 DRUG INTERACTIONS

Blue dyes used for SLN mapping procedures generate a fluorescent signal that interferes with the signal from LUMISIGHT when injected into the breast prior to imaging with LUMISIGHT. The potential of other dyes to interfere with LUMISIGHT imaging has not been evaluated. Avoid administration of dyes used for SLN mapping procedure before imaging the lumpectomy cavity in patients receiving LUMISIGHT.

8 USE IN SPECIFIC POPULATIONS

8.1 Pregnancy

Risk Summary

There are no available data on pegulicianine use in pregnant women to evaluate for a drug associated risk of major birth defects, miscarriage, or other adverse maternal or fetal outcomes. Animal reproduction studies were not conducted with pegulicianine.

The background risk of major birth defects and miscarriage for the indicated population is unknown. All pregnancies have a background risk of birth defect, loss, or other adverse outcomes. In the U.S. general population, the estimated background risk of major birth defects and miscarriage in clinically recognized pregnancies is 2% to 4% and 15% to 20%, respectively.

8.2 Lactation

Risk Summary

There are no data on the presence of pegulicianine or its metabolites in either human or animal milk, the effects on the breastfed infant, or the effects on milk production. The developmental and health benefits of breastfeeding should be considered along with the mother’s clinical need for LUMISIGHT and any potential adverse effects on the breastfed infant from LUMISIGHT or from the underlying maternal condition.

8.4 Pediatric Use

Safety and effectiveness of LUMISIGHT in pediatric patients have not been established.

8.5 Geriatric Use

Of 703 patients in clinical studies of LUMISIGHT for breast cancer who received the recommended dose of 1 mg/kg, 44% were 65 years of age and over, while 8% were 75 and over. No overall differences in safety or effectiveness have been observed between these patients and younger adult patients.

11 DESCRIPTION

LUMISIGHT (pegulicianine for injection) is an optical imaging agent for intravenous use.

The chemical name of pegulicianine acetate is N-[6-(1-{2-[3,6-bis(2,3-dihydro-1H-indol-1-yl)xanthylium-9-yl]benzene-1-sulfonyl}piperidine-4-carboxamido)hexanoyl]glycylglycyl-L-arginyl-N6-(6-{2-[(1E,3E,5Z)-5-(1-ethyl-3,3-dimethyl-5-sulfonato-1,3-dihydro-2H-indol-2-ylidene)penta-1,3-dien-1-yl]-3,3-dimethyl-5-sulfonato-3H-indol-1-ium-1-yl}hexanoyl)-Llysyl-[2-(2-aminoethoxy)ethoxy]acetyl-S-[(3RS)-1-{6-[α-methylpoly(oxyethylene)-ω-amino]-6-oxohexyl}-2,5-dioxopyrrolidin-3-yl]-L-cysteinamide acetate with a molecular formula of C116H147N19O23S4(C2H4O)n, with n of approximately 450, a molecular weight of 20-25 kDa, and the following structural formula:

Figure 1: Molecular structure of pegulicianine acetate

LUMISIGHT is supplied as a sterile, dark blue lyophilized powder. Each vial contains 40 mg of pegulicianine (equivalent to 40.1 mg of pegulicianine acetate) and the following inactive ingredients: 3.2 mg of dibasic sodium phosphate heptahydrate, 39.5 mg of mannitol, and 3.8 mg of monobasic sodium phosphate monohydrate to permit withdrawal of 3.9 mL of pegulicianine 10 mg/mL upon reconstitution with 4 mL of 0.45% sodium chloride injection, USP. The pH of the reconstituted solution is 6 to 7.

12 CLINICAL PHARMACOLOGY

12.1 Mechanism of Action

Pegulicianine is a prodrug that is optically inactive when intact and produces a fluorescent signal after its peptide chain is cleaved by cathepsins and matrix metalloproteases (MMPs). The levels of these enzymes are higher in and around tumor and tumor-associated cells than normal cells.

This enzymatic cleavage results in “fragment 2” and “fragment 3”, which are optically active metabolites that emit fluorescence, as well as “fragment 1” containing the fluorescence quencher that keeps the intact molecule optically inactive. “Fragment 2” and “fragment 3” absorb light in the visible light region with a peak absorption at 650 nm and fluoresce with a peak emission at 675 nm.

12.2 Pharmacodynamics

The relationships between the plasma concentrations of the optically active metabolites and the time course of pharmacodynamic response have not been fully characterized.

12.3 Pharmacokinetics

Elimination

Metabolism

Pegulicianine is cleaved by cathepsins and matrix metalloproteases to the active metabolites “fragment 2” and “fragment 3.” Pegulicianine undergoes minimal hepatic metabolism in vitro.

Excretion

Pegulicianine excretion pathway in humans is unknown. Observed blue/green discoloration of urine (chromaturia) in subjects receiving pegulicianine suggests that pegulicianine and/or its metabolites may be excreted renally.

Specific Populations

Patients with Renal Impairment

Mild renal impairment (RI) does not appear to have a clinically meaningful effect on the pharmacokinetics, safety, and efficacy of pegulicianine and fragment 3; fragment 2 data are not available. The effect of moderate or severe RI on the pharmacokinetics, safety, and efficacy of pegulicianine, fragment 2, and fragment 3 has not been evaluated.

13 NONCLINICAL TOXICOLOGY

13.1 Carcinogenesis, Mutagenesis, Impairment of Fertility

No studies in animals have been conducted to evaluate the carcinogenic potential of pegulicianine.

The nonfluorescent major metabolite of pegulicianine was not mutagenic in nonclinical tests, i.e., in vitro reverse mutation test in bacteria (Ames test), in vitro chromosomal aberration test in human peripheral blood lymphocytes, and in vivo (mice) micronucleus test after intravenous doses up to 11.24 mg/kg (225 times the pegulicianine clinical dose of 1 mg/kg).

No reproductive and developmental toxicity studies in animals have been performed to evaluate the effects of pegulicianine on fertility.

14 CLINICAL STUDIES

The efficacy and safety of LUMISIGHT for the intraoperative detection of cancerous tissue within the resection cavity following removal of the primary specimen during lumpectomy surgery in patients with breast cancer were evaluated in a randomized, multicenter, intra-patient controlled clinical trial NCT03686215. A total of 406 adult patients with confirmed invasive breast cancer, ductal carcinoma in situ (DCIS), or both received 1 mg/kg LUMISIGHT by intravenous injection 2 hours to 6 hours prior to imaging with the Lumicell DVS. Among them, 357 patients underwent LUMISIGHT-guided imaging after completion of the standard of care lumpectomy procedure. Patients who received neoadjuvant chemotherapy or radiotherapy prior to surgery were excluded from study. After the standard of care (SOC) lumpectomy was completed, the lumpectomy cavity was divided into six regions based on anatomic orientation and each region was imaged with the Lumicell DVS. When positive fluorescence signal was detected, the tissue was resected with a cavity shave procedure and the region was re-imaged. A maximum of two LUMISIGHT-guided shaves were obtained from a single region. Histopathology analysis of excised tissue served as the reference standard. Cavity regions that did not have a LUMISIGHT-guided cavity shave or tissue from a second surgery for a reference standard were assigned the margin status of the corresponding outermost surface of the lumpectomy specimen or SOC cavity shave, with a positive margin defined as tumor on ink for invasive cancers (with or without DCIS) or within 2 mm of the inked margin for DCIS alone.

The mean age of patients was 62 years (range: 36 years to 83 years). Distribution by race was 82% White, 7% Black or African American, 6% Asian, and 5% other. Distribution by ethnicity was 3% Hispanic/Latino, 94% non-Hispanic/Latino, and 3% unknown or unreported. In the study group, 70% of patients had invasive ductal carcinoma (with or without DCIS), 20% had DCIS only, 10% had invasive lobular carcinoma (with or without DCIS), and <1% had both invasive ductal and invasive lobular carcinoma.

The study assessed the proportion of patients receiving LUMISIGHT who had residual cancer detected and removed using the Lumicell DVS after completion of SOC lumpectomy. One hundred and sixty-six (166) of 357 (46%) patients had at least one LUMISIGHT-guided shave. A total of 27 of 357 patients had residual cancer confirmed by histopathology in at least one LUMISIGHT-guided shave (7.6%; 95% CI: 5.0%, 10.8%).

Table 1 shows sensitivity and specificity of LUMISIGHT for residual breast cancer after completion of SOC lumpectomy calculated from the 2,346 evaluable images in the study. Regions of the lumpectomy cavity from which LUMISIGHT-guided shaves were taken contributed more than one image to the analysis.

A total of 155 of 357 (43%) patients had at least one false positive image, and 28 of 357 (8%) patients had at least one false negative image. Among the 166 patients with at least one LUMISIGHT-guided shave, the mean total LUMISIGHT-guided shave volume was 22 cm^3 ± 20 cm^3, accounting for 20% ± 15% of the total volume of resection.

After completion of SOC lumpectomy, prior to LUMISIGHT-guided tissue removal, 62 of 357 patients (17%) had at least one cancer-positive margin. After LUMISIGHT-guided surgery, 9 of these 62 (15%) patients changed to having all cancer-negative margins, and 2 of the remaining 295 (1%) patients changed from having all cancer-negative margins to having at least one cancer-positive margin.

16 HOW SUPPLIED/STORAGE AND HANDLING

How supplied

LUMISIGHT (pegulicianine) for injection is supplied as a dark blue lyophilized powder for reconstitution in a clear, glass single-dose vial in cartons of 10 vials (NDC 82292-040-10). After reconstitution, each vial delivers 39 mg pegulicianine.

Storage and Handling

Store vials of LUMISIGHT frozen at -25°C to -15°C (-13°F to 5°F) in the original carton to protect from light.

17 PATIENT COUNSELING INFORMATION

Anaphylaxis and Other Serious Hypersensitivity Reactions

Inform patients of the risk of hypersensitivity reactions, including anaphylaxis, and instruct them to alert healthcare providers immediately if they experience signs and symptoms of a hypersensitivity reaction [see Warnings and Precautions (5.1)].

Urine Discoloration

Inform patients that LUMISIGHT may cause blue discoloration of the urine that in most cases will resolve within 48 hours [see Adverse Reactions (6.1)].

Skin Discoloration After Extravasation

Inform patients that if extravasation occurs, it may result in blue discoloration of the skin at the injection site that will be evident for several weeks [see Adverse Reactions (6.1)].

Manufactured for:
Lumicell, Inc.
275 Washington Street, Suite 200
Newton, MA 02458

LUMISIGHT™ and Lumicell™ are trademarks of Lumicell, Inc.

©2024 Lumicell, Inc. All rights reserved.

PRINCIPAL DISPLAY PANEL - Vial Label

Rx Only
NDC 82292-040-01

LUMISIGHT
(pegulicianine for injection)
39 mg per vial

Single-Dose vial.
Discard unused portion.

For intravenous use after reconstitution with
0.45% Sodium Chloride Injection, USP

After reconstitution, store at room temperature 20°C to 25°C
(68°F to 77°F) and use within 4 hours or store refrigerated at 2°C
to 8°C (35°F to 46°F) and use within 24 hours. Protect from light.

PRINCIPAL DISPLAY PANEL - Carton Label

Rx Only
NDC 82292-040-10

LUMISIGHT
(pegulicianine for injection)
39 mg per vial

Single-Dose vial.
Discard unused portion.

For intravenous use after reconstitution with
0.45% Sodium Chloride Injection, USP

10 single-dose vials. Discard unused portion.

Storage: Prior to reconstitution, store frozen at -25°C to -15°C (-13°F to 5°F). Store in original carton to protect from light.

Recommended Dose: See Prescribing Information.

Each vial contains 40 mg of pegulicianine (equivalent to 40.1 mg of pegulicianine acetate) and the following inactive
ingredients: 3.2 mg of dibasic sodium phosphate heptahydrate, 39.5 mg of mannitol, and 3.8 mg of monobasic sodium
phosphate monohydrate.

Reconstitution: Reconstitute each vial with 4 mL of 0.45% Sodium Chloride Injection, USP to permit withdrawal of 3.9 mL
of pegulicianine 10 mg/mL.

After reconstitution: Store vial at room temperature at 20°C to 25°C (68°F to 77°F) and use within 4 hours,
or store refrigerated at 2°C to 8°C (35°F to 46°F) and use within 24 hours. Protect from light.